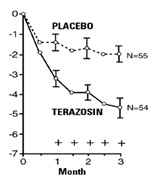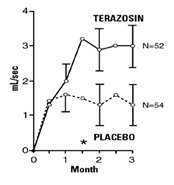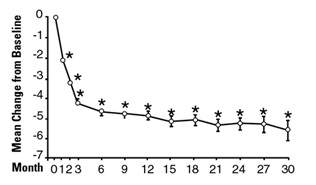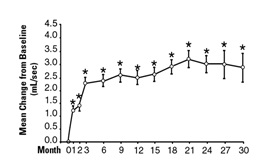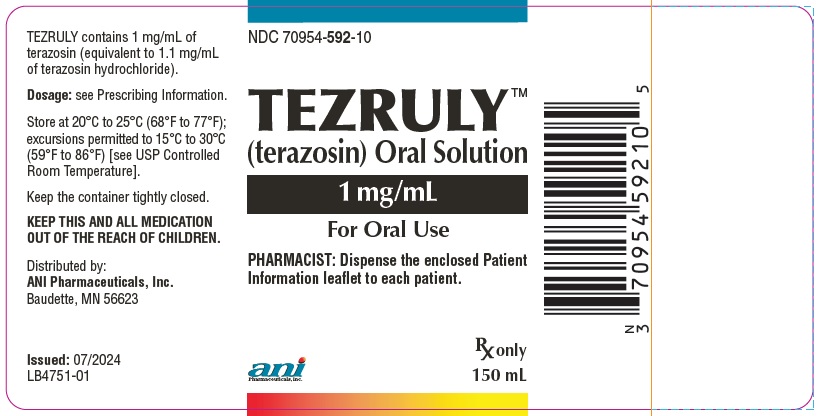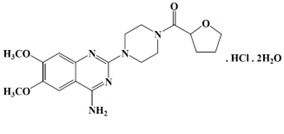 DRUG LABEL: TEZRULY
NDC: 70954-592 | Form: SOLUTION
Manufacturer: ANI Pharmaceuticals, Inc.
Category: prescription | Type: Human Prescription Drug Label
Date: 20250418

ACTIVE INGREDIENTS: TERAZOSIN HYDROCHLORIDE 1 mg/1 mL
INACTIVE INGREDIENTS: ALCOHOL; ANHYDROUS CITRIC ACID; GLYCERIN; METHYLPARABEN; PROPYLPARABEN; WATER; TRISODIUM CITRATE DIHYDRATE; SUCRALOSE

HIGHLIGHTS OF PRESCRIBING INFORMATION

These highlights do not include all the information needed to use TEZRULY safely and effectively. See full prescribing information for TEZRULY.
TEZRULY (terazosin) oral solution
Initial U.S. Approval: 1993

1 INDICATIONS & USAGE

TEZRULYTM (terazosin) is an alpha-1 adrenoceptor antagonist indicated for:

- The treatment of signs and symptoms of benign prostatic hyperplasia (BPH) (1.1)
- The treatment of hypertension alone or with other antihypertensive agents, to lower blood pressure. Lowering blood pressure reduces the risk of fatal and nonfatal cardiovascular events, primarily strokes and myocardial infarction. (1.2)

2 DOSAGE & ADMINISTRATION

- For the treatment of BPH: Initiate therapy at 1 mg orally once daily at bedtime. Titrate the dose upwards step-wise from 2 mg to 10 mg once daily. Doses of 10 mg once daily are generally required for a clinical response. Data is insufficient to support doses greater than 20 mg once daily. (2.1)
- For the treatment hypertension: Initiate therapy at 1 mg orally once daily at bedtime. Usual recommended dose range is 1 mg to 5 mg once daily. If response is substantially diminished at 24 hours, increase the dose or use twice daily. Dose may be titrated as needed up to 20 mg once daily. (2.2)
- If terazosin is discontinued for more than a few days, restart using the initial dosing regimen. (2.1)

3 DOSAGE FORMS & STRENGTHS

- Oral solution: 1 mg/mL of terazosin (3)

4 CONTRAINDICATIONS

Hypersensitivity to terazosin hydrochloride or any other ingredient in TEZRULY. (4)

5 WARNINGS AND PRECAUTIONS

- Syncope and “First-dose” Effect: Advise patients about the possibility of symptoms related to postural hypotension and to avoid situations where injury could result should syncope occur, especially when starting TEZRULY. (5.1)
- Orthostatic Hypotension: Dizziness, lightheadedness, and palpitations can occur with use of TEZRULY. Advise patients to take their first dose of TEZRULY at bedtime and to avoid driving or hazardous tasks for 12 hours after the first dose, after a dosage increase, and after interruption of therapy when treatment is resumed. (5.2)
- Risk of Hypotension with Concomitant Use of Other Antihypertensive Agents and Phospodiesterase Type 5 Inhibitors (PDE5-I): Concomitant administration of TEZRULY with antihypertensives or phosphodiesterase-5 (PDE-5) inhibitors can result in additive blood pressure lowering effects and symptomatic hypotension (5.3).
- Priapism: Advise patients about the possibility and seriousness of priapism. (5.4)
- Intraoperative Floppy Iris Syndrome: Advise patients considering cataract surgery to tell their ophthalmologist that they have taken terazosin as Intraoperative Floppy Iris Syndrome as been observed during cataract surgery in some patients. (5.5)
- Prostatic Cancer: Screen for the presence of prostatic cancer prior to treatment for BPH and at regular intervals afterwards. (5.6)

6 ADVERSE REACTIONS

- In treatment of BPH, the most common adverse reactions (≥1% of patients and at a higher incidence than placebo) were asthenia, flu syndrome, postural hypotension, nausea, somnolence, vertigo, dyspnea, nasal congestion/rhinitis, blurred vision/amblyopia and erectile dysfunction. (6.1)
- In treatment of hypertension, the most common adverse reactions where the incidence on terazosin was ≥ 5%, where the incidence on terazosin was at least 2% and greater than placebo or where the reaction was of particular interest were asthenia, back pain, pain in the extremities, headache, palpitations, postural hypotension, tachycardia, nausea, edema, peripheral edema, weight gain, depression, dizziness, libido, decreased, nervousness, paresthesia, somnolence, dyspnea, nasal congestion, sinusitis, blurred vision, and erectile dysfunction. (6.1)

To report SUSPECTED ADVERSE REACTIONS, contact ANI Pharmaceuticals, Inc. at 1-855-204-1431 or FDA at 1-800-FDA-1088 or www.fda.gov/medwatch.

7 DRUG INTERACTIONS

- Co-administration of verapamil with terazosin increases the systemic exposure of terazosin and may lead to hypotension. Dosage reduction and re-titration of either agent may be necessary. (7)

FULL PRESCRIBING INFORMATION

1 INDICATIONS & USAGE

1.1 Benign Prostatic Hyperplasia

TEZRULY is indicated for the treatment of the signs and symptoms of benign prostatic hyperplasia (BPH) in adult males [see Clinical Studies (14.1)].

1.2 Hypertension

TEZRULY is indicated for the treatment of hypertension, to lower blood pressure in adults [see Clinical Studies (14.2)]. Lowering blood pressure reduces the risk of fatal and non-fatal cardiovascular events, primarily strokes and myocardial infarctions. These benefits have been seen in controlled trials of antihypertensive drugs from a wide variety of pharmacologic classes.

Control of high blood pressure should be part of comprehensive cardiovascular risk management, including, as appropriate, lipid control, diabetes management, antithrombotic therapy, smoking cessation, exercise, and limited sodium intake. Many patients will require more than one drug to achieve blood pressure goals. For specific advice on goals and management, see published guidelines, such as those of the National High Blood Pressure Education Program’s Joint National Committee on Prevention, Detection, Evaluation, and Treatment of High Blood Pressure (JNC).

Numerous antihypertensive drugs, from a variety of pharmacologic classes and with different mechanisms of action, have been shown in randomized controlled trials to reduce cardiovascular morbidity and mortality, and it can be concluded that it is blood pressure reduction, and not some other pharmacologic property of the drugs, that is largely responsible for those benefits. The largest and most consistent cardiovascular outcome benefit has been a reduction in the risk of stroke, but reductions in myocardial infarction and cardiovascular mortality also have been seen regularly.

Elevated systolic or diastolic pressure causes increased cardiovascular risk, and the absolute risk increase per mmHg is greater at higher blood pressures, so that even modest reductions of severe hypertension can provide substantial benefit. Relative risk reduction from blood pressure reduction is similar across populations with varying absolute risk, so the absolute benefit is greater in patients who are at higher risk independent of their hypertension (for example, patients with diabetes or hyperlipidemia), and such patients would be expected to benefit from more aggressive treatment to a lower blood pressure goal.

Some antihypertensive drugs have smaller blood pressure effects (as monotherapy) in black patients, and many antihypertensive drugs have additional approved indications and effects (e.g., on angina, heart failure, or diabetic kidney disease). These considerations may guide selection of therapy.

TEZRULY may be used alone or in combination with other antihypertensive agents.

2 DOSAGE & ADMINISTRATION

2.1 Recommended Dosage for Benign Prostatic Hyperplasia

Initial Dose: 1 mg orally once daily at bedtime. This dose should not be exceeded as an initial dose. Closely follow patients during initial administration in order to minimize the risk of severe hypotensive response, including syncope. For administration instructions, see Dosage and Administration (2.3).

Subsequent Doses: The dose should be increased in a stepwise fashion from 2 mg to 10 mg orally once daily to achieve the desired improvement of symptoms and/or flow rates. Doses of 10 mg once daily are generally required for a clinical response. Therefore, treatment with 10 mg for a minimum of 4 weeks to 6 weeks may be required to assess whether a beneficial response has been achieved. Although some patients responded to 20 mg per daily, data are insufficient to draw definitive conclusions about this dose. There are insufficient data to support the use of doses higher than 20 mg daily. If TEZRULY is discontinued for more than a few days, therapy should be restarted using the initial dosing regimen. For administration instructions, see Dosage and Administration (2.3).

2.2 Recommended Dosage for Hypertension

- Initial Dose: 1 mg orally once daily at bedtime. Do not exceed the initial dosing regimen to minimize the potential for severe hypotensive effects, including syncope. For administration instructions, see Dosage and Administration (2.3).
- Subsequent Doses: Slowly increase the dose to achieve the desired blood pressure response. The usual recommended dose range is 1 mg to 5 mg orally once daily; however, some patients may benefit from doses as high as 20 mg per day. Doses over 20 mg do not appear to provide further blood pressure effect and doses over 40 mg have not been studied. Blood pressure should be monitored at the end of the dosing interval to ensure control throughout the dosing interval. It may also be helpful to measure blood pressure 2 hours to 3 hours after dosing to see if the maximum and minimum responses are similar, and to evaluate symptoms such as dizziness or palpitations which can result from excessive hypotensive response. If response is substantially diminished at 24 hours, consider increasing the dose or use a twice daily dosing regimen. In clinical trials, except for the initial dose, the dose was given in the morning. If TEZRULY is discontinued for more than a few days, therapy should be restarted using the initial dosing regimen. For administration instructions, see Dosage and Administration (2.3).

TEZRULY may be used alone or in combination with other antihypertensive agents. Adjust the dose of TEZRULY and the dose frequency (every 12 hours or 24 hours) based on the patient’s individual blood pressure response.

2.3 Administration Information

Take TEZRULY orally with or without food.

A calibrated measuring device, such as an oral syringe or oral dosing cup, is recommended to measure and deliver the prescribed dose accurately. A household measuring cup, teaspoon, or tablespoon is not an adequate measuring device.

3 DOSAGE FORMS & STRENGTHS

Oral solution: 1 mg/mL terazosin, clear, cherry flavored solution, free from visible particulate matter.

4 CONTRAINDICATIONS

TEZRULY is contraindicated in patients known to be hypersensitive to terazosin or any component of TEZRULY.

5 WARNINGS AND PRECAUTIONS

5.1 Syncope and ‘‘First-dose’’ Effect

TEZRULY, like other alpha-1-adrenoceptors antagonists, can cause marked lowering of blood pressure, especially postural hypotension, and syncope in association with the first dose or first few days of therapy [see Warnings and Precautions (5.2)]. A similar effect can be anticipated if therapy is interrupted for several days and then restarted. Syncope has also been reported with other alpha-1-adrenoceptors antagonists in association with rapid dosage increases or the introduction of another antihypertensive drug. Syncope is believed to be due to an excessive postural hypotensive effect, although occasionally the syncopal episode has been preceded by a bout of severe supraventricular tachycardia with heart rates of 120-160 beats per minute. Additionally, the possibility of the contribution of hemodilution to the symptoms of postural hypotension should be considered.

To decrease the likelihood of syncope or excessive hypotension, initiate treatment with a 1 mg dose of terazosin, given at bedtime. Higher doses (e.g., 2 to 10 mg) are not indicated as initial therapy. Then slowly increase the dose [see Dosage and Administration (2.1 and 2.2)], and add additional antihypertensive agents with caution. Advise patients to avoid situations, such as driving or hazardous tasks, where injury could result should syncope occur during initiation of therapy.

In early investigational studies, where increasing single doses up to 7.5 mg were given at 3-day intervals, tolerance to the first dose phenomenon did not necessarily develop and the ‘‘first-dose” effect could be observed at all doses. Syncopal episodes occurred in 3 of the 14 subjects given terazosin at doses of 2.5, 5 and 7.5 mg, which are higher than the recommended initial dose; in addition, severe orthostatic hypotension (blood pressure falling to 50/0 mmHg) was seen in two others and dizziness, tachycardia, and lightheadedness occurred in most subjects. These adverse effects all occurred within 90 minutes of dosing.

In three placebo-controlled BPH studies 1, 2, and 3 [see Clinical Pharmacology (12)], the incidence of postural hypotension in the terazosin treated patients was 5.1%, 5.2%, and 3.7% respectively.

In multiple dose clinical trials involving nearly 2000 hypertensive patients treated with terazosin, syncope was reported in about 1% of patients. Syncope was not necessarily associated only with the first dose.

If syncope occurs, place the patient in a recumbent position and treat supportively as necessary. There is evidence that the orthostatic effect of terazosin is greater, even in chronic use, shortly after dosing. The risk of the events is greatest during the initial seven days of treatment but continues at all time intervals.

5.2 Orthostatic Hypotension

While syncope is the most severe orthostatic effect of terazosin, other symptoms of lowered blood pressure [see Warnings and Precautions (5.1)], such as dizziness, lightheadedness and palpitations were more common and occurred in some 28% of patients in clinical trials of hypertension. In BPH clinical trials, 21% of the patients experienced one or more of the following: dizziness, hypotension, postural hypotension, syncope, and vertigo. Patients with occupations in which such events represent potential problems should be treated with particular caution. Advise patients to take their first dose of TEZRULY at bedtime and to avoid driving or hazardous tasks for 12 hours after the first dose, after a dosage increase, and after interruption of therapy when treatment is resumed.

5.3 Risk of Hypotension with Concomitant Use of Other Antihypertensive Agents and Phosphodiesterase Type 5 Inhibitors (PDE5-I)

Concomitant use of TEZRULY with other anti-hypertensive agents, especially the calcium channel blocker verapamil, can increase the risk of hypotension. To reduce the risk of hypotension, dosage reduction and re-titration of either agent may be necessary [see Warnings and Precautions (5.1 and 5.2)]. Hypotension has been reported when terazosin has been used with phosphodiesterase-5 (PDE-5) inhibitors. Therefore, PDE-5 inhibitor therapy should be initiated at the lowest dose in patients taking TEZRULY.

5.4 Priapism

Rarely (probably less than once in every several thousand patients) terazosin and other alpha-1-selective adrenoceptor antagonist have been associated with priapism (painful penile erection, sustained for hours and unrelieved by sexual intercourse or masturbation). Because this condition can lead to permanent impotence if not promptly treated, advise patients about the seriousness of the condition and the need to seek immediate medical attention at an emergency room.

5.5 Prostatic Cancer

Carcinoma of the prostate and BPH present with many of the same symptoms and frequently co-exist. Therefore, examine patients thought to have BPH prior to starting TEZRULY therapy to rule out the presence of carcinoma of the prostate.

5.6 Intraoperative Floppy Iris Syndrome

Intraoperative floppy iris syndrome (IFIS) has been observed during cataract surgery in some patients on/or previously treated with alpha-1-adrenoceptor antagonists. This variant of small pupil syndrome is characterized by the combination of a flaccid iris that billows in response to intraoperative irrigation currents, progressive intraoperative miosis despite preoperative dilation with standard mydriatic drugs, and potential prolapse of the iris toward the phacoemulsification incisions. The patient’s ophthalmologist should be prepared for possible implementation of intraoperative preventive measures and modifications to surgical techniques during phacoemulsification surgery to reduce overall complication rates. There does not appear to be a benefit of stopping alpha-1-adrenoceptor antagonists therapy prior to cataract surgery.

5.7 Laboratory Tests

Small but statistically significant decreases in hematocrit, hemoglobin, white blood cells, total protein and albumin were observed in controlled clinical trials. These laboratory findings suggested the possibility of hemodilution. Treatment with terazosin for up to 24 months had no significant effect on prostate specific antigen (PSA) levels.

6 ADVERSE REACTIONS

The following clinically significant adverse reactions are described elsewhere in the labeling:

- Syncope and ‘‘First-dose’’ Effect [see Warnings and Precautions (5.1)]
- Orthostatic Hypotension [see Warnings and Precautions (5.2)]
- Priapism [see Warnings and Precautions (5.3)]
- Intraoperative Floppy Iris Syndrome [see Warnings and Precautions (5.5)]

6.1 Clinical Trials Experience

Because clinical studies are conducted under widely varying conditions, adverse reactions rates observed in the clinical studies of a drug cannot be directly compared to rates in the clinical studies of another drug and may not reflect the rates observed in practice.

Benign Prostatic Hyperplasia

The incidence rates presented below are based on combined data from six placebo-controlled trials involving once-daily administration of terazosin at doses ranging from 1 to 20 mg. Table 1 summarizes those adverse events reported for patients in these trials when the incidence rate in the terazosin group was at least 1% and was greater than that for the placebo group, or where the reaction is of clinical interest.

Asthenia, postural hypotension, dizziness, somnolence, nasal congestion/rhinitis, and impotence were the only events that were significantly (p ≤ 0.05) more common in patients receiving terazosin than in patients receiving placebo. The incidence of urinary tract infection was significantly lower in the patients receiving terazosin than in patients receiving placebo. An analysis of the incidence rate of hypotensive adverse reactions [see Warnings and Precautions (5.1, 5.2)] adjusted for the length of drug treatment has shown that the risk of the reactions is greatest during the initial seven days of treatment but continues at all time intervals.

Table 1. Adverse Reactions Reported During Placebo-Controlled Studies of Terazosin in Patients with Benign Prostatic Hyperplasia
Body System | Terazosin (N=636) % | Placebo (N=360) %
BODY AS A WHOLE
†Asthenia | 7* | 3
Flu Syndrome | 2 | 2
Headache | 5 | 6
CARDIOVASCULAR SYSTEM
Hypotension | 1 | 1
Palpitations | 1 | 1
Postural Hypotension | 4* | 1
Syncope | 1 | 0
DIGESTIVE SYSTEM
Nausea | 2 | 1
METABOLIC AND NUTRITIONAL DISORDERS
Peripheral Edema | 1 | 0
Weight Gain | 1 | 0
NERVOUS SYSTEM
Dizziness | 9* | 4
Somnolence | 4 | 2
Vertigo | 1 | 0
RESPIRATORY SYSTEM
Dyspnea | 2 | 1
Nasal Congestion/Rhinitis | 2* | 0
UROGENITAL SYSTEM
Erectile Dysfunction | 2* | 1
Urinary Tract Infection | 1 | 4*
† Includes weakness, tiredness, lassitude and fatigue.
* p ≤ 0.05, comparison between groups.

Additional adverse reactions have been reported, but these are, in general, not distinguishable from symptoms that might have occurred in the absence of exposure to terazosin. The safety profile of patients treated in the long-term open-label study was similar to that observed in the controlled studies.

Adverse reactions were usually transient and mild or moderate in intensity, but sometimes were serious enough to interrupt treatment. In the placebo-controlled clinical trials, the rates of premature termination due to adverse reactions were not statistically different between the placebo and terazosin groups. Adverse reactions that were bothersome, reported as the reason for discontinuation of therapy by at least 0.5% of the terazosin group and reported more often than in the placebo group are shown in Table 2.

Table 2. Discontinuation Rates During Placebo-Controlled Studies of Terazosin in Patients with Benign Prostatic Hyperplasia
Body System | Terazosin (N=636) % | Placebo (N=360) %
BODY AS A WHOLE
Fever | 0.5% | 0.0%
Headache | 1.1% | 0.8%
CARDIOVASCULAR SYSTEM
Postural Hypotension | 0.5% | 0.0%
Syncope | 0.5% | 0.0%
DIGESTIVE SYSTEM
Nausea | 0.5% | 0.3%
NERVOUS SYSTEM
Dizziness | 2.0% | 1.1%
Vertigo | 0.5% | 0.0%
RESPIRATORY SYSTEM
Dyspnea | 0.5% | 0.3%
SPECIAL SENSES
Blurred Vision/Amblyopia | 0.6% | 0.0%
UROGENITAL SYSTEM
Urinary Tract Infection | 0.6% | 0.0%

Hypertension

The prevalence rates presented below are based on combined data from fourteen placebo-controlled studies involving once-daily administration of terazosin, as monotherapy or in combination with other antihypertensive agents, at doses ranging from 1 to 40 mg. Table 3 summarizes those adverse reactions reported for patients in these trials where the prevalence rate in the terazosin group was at least 5%, where the prevalence rate for the terazosin group was at least 2% and was greater than the prevalence rate for the placebo group, or where the reaction is of particular interest. Asthenia, blurred vision, dizziness, nasal congestion, nausea, peripheral edema, palpitations and somnolence were the only symptoms that were significantly (p < 0.05) more common in patients receiving terazosin than in patients receiving placebo. Similar adverse reaction rates were observed in placebo-controlled monotherapy trials.

Table 3. Adverse Reactions Reported During Placebo-Controlled Studies of Terazosin in Patients with Hypertension
Body System | Terazosin (N=859) % | Placebo (N=506) %
BODY AS A WHOLE
†Asthenia | 11* | 4
Back Pain | 2 | 1
CARDIOVASCULAR SYSTEM
Palpitations | 4* | 1
Postural Hypotension | 1 | 0
Tachycardia | 2 | 1
DIGESTIVE SYSTEM
Nausea | 4* | 1
METABOLIC AND NUTRITIONAL DISORDERS
Peripheral Edema | 6* | 2
Weight Gain | 1 | 0
MUSCULOSKELETAL SYSTEM
Pain-Extremities | 4 | 3
NERVOUS SYSTEM
Dizziness | 19* | 8
Libido Decreased | 1 | 0
Paresthesia | 3 | 1
Somnolence | 5* | 3
RESPIRATORY SYSTEM
Dyspnea | 3 | 2
Nasal Congestion | 6* | 3
Sinusitis | 3 | 1
SPECIAL SENSES
Blurred Vision | 2* | 0
UROGENITAL SYSTEM
Erectile Dysfunction | 1 | 1
† Includes weakness, tiredness, lassitude and fatigue.
* Statistically significant at p=0.05 level.

The following adverse reactions associated with the use of terazosin were identified in clinical studies (≥1%) or during post-approval use of terazosin. Because some of these reactions were reported voluntarily from a population of uncertain size, it is not always possible to reliably estimate their frequency or establish a causal relationship to drug exposure:

Body as a Whole: edema, facial edema;

Cardiovascular System: chest pain, arrhythmia, vasodilation;

Digestive System: abdominal pain, constipation, diarrhea, dry mouth, dyspepsia, flatulence, vomiting;

Metabolic/Nutritional Disorders: gout;

Musculoskeletal System: arthralgia, arthritis, joint disorder, myalgia, neck pain, shoulder pain;

Nervous System: anxiety, insomnia, nervousness, depression;

Respiratory System: bronchitis, cold symptoms, epistaxis, increased cough, pharyngitis;

Skin and Appendages: pruritus, rash, sweating;

Special Senses: abnormal vision, conjunctivitis, tinnitus;

Urogenital System: urinary frequency, urinary incontinence primarily reported in postmenopausal women;

Adverse reactions were usually mild or moderate in intensity but sometimes were serious enough to interrupt treatment. The adverse reactions that were most bothersome, reported as reason for discontinuation therapy by at least 0.5% of the terazosin group and being reported more often than in the placebo group are shown in Table 4.

Table 4. Discontinuations During Placebo-Controlled Studies of Terazosin in Patients with Hypertension
Body System | Terazosin (N=859) % | Placebo (N=506) %
BODY AS A WHOLE
Asthenia | 1.6% | 0.0%
Headache | 1.3% | 1.0%
CARDIOVASCULAR SYSTEM
Palpitations | 1.4% | 0.2%
Postural Hypotension | 0.5% | 0.0%
Syncope | 0.5% | 0.2%
Tachycardia | 0.6% | 0.0%
DIGESTIVE SYSTEM
Nausea | 0.8% | 0.0%
METABOLIC AND NUTRITIONAL DISORDERS
Peripheral Edema | 0.6% | 0.0%
NERVOUS SYSTEM
Dizziness | 3.1% | 0.4%
Paresthesia | 0.8% | 0.2%
Somnolence | 0.6% | 0.2%
RESPIRATORY SYSTEM
Dyspnea | 0.9% | 0.6%
Nasal Congestion | 0.6% | 0.0%
SPECIAL SENSES
Blurred Vision | 0.6% | 0.0%

6.2 Post-marketing Experience

The following adverse reactions have been identified during postapproval use of terazosin. Because these reactions are reported voluntarily from a population of uncertain size, it is not always possible to reliably estimate their frequency or establish a causal relationship to drug exposure.

Blood and Lymphatic System: thrombocytopenia

Cardiovascular System: atrial fibrillation

Skin and Appndages: allergic reactions, including anaphylaxis

Urogenital System: priapism

During cataract surgery, a variant of small pupil syndrome known as intraoperative floppy iris syndrome (IFIS) has been reported in association with alpha-1 antagonist therapy [see Warnings and Precautions (5.5)].

7 DRUG INTERACTIONS

Co-administration of verapamil with terazosin increases the systemic exposure of terazosin [see Clinical Pharmacology (12.3)], which may increase the risk of hypotenstion. To reduce the risk of hypotension, dosage reduction and re-titration of either agent may be necessary [see Warnings and Precautions (5.3)].

8 USE IN SPECIFIC POPULATIONS

8.1 Pregnancy

Risk Summary

The limited available data on terazosin use in pregnant women are insufficient to inform a drug-associated risk of major birth defects, miscarriage, or other adverse maternal or fetal outcomes.

In animal reproduction studies, no adverse developmental effects were observed when terazosin was orally administered to pregnant rats and rabbits during the period of organogenesis at doses of up to 230 and 60 times, respectively, the maximum recommended human dose on a body surface area (mg/m^2) basis. In the rat and rabbit oral doses at 230 and 60 times, respectively, the maximum recommended human dose on a body surface area basis, reduced fetal survival was observed [see Data].

The estimated background risk of major birth defects and miscarriage for the indicated population is unknown. In the U.S. general population, the estimated background risk of major birth defects and miscarriage in clinically recognized pregnancies is 2 to 4% and 15 to 20%, respectively.

Data

Animal Data

Studies in rats and rabbits at oral doses up to 230 and 60 times, respectively, the maximum recommended human dose on a body surface area (mg/m^2) basis, have revealed no evidence of adverse developmental effects. In rats, fetal resorptions were observed at 480 mg/kg/day, approximately 230 times the maximum recommended human dose on a body surface area basis. In rabbits,. increased fetal resorptions, decreased fetal weight and an increased number of supernumerary ribs were observed at 60 mg/kg/day, 60 times the maximum recommended human dose on a body surface area basis. These findings (in both species) were most likely secondary to maternal toxicity.

In a peri- and post-natal development study in rats, significantly more pups died at 120 mg/kg/day (60 times the maximum recommended human dose on a body surface area basis) than in the control group during the three-week postpartum period.

8.2 Lactation

Risk Summary

There are no available data on the presence of terazosin in human milk, effects on the breastfed infant, or the effects on milk production.

8.3 Females and Males of Reproductive Potential

Infertility

Males

Possible effects on male fertility could be observed based on findings in rats at exposures that were at least 15 times higher than at the maximum recommended human dose on a body surface area basis. The clinical relevance of this finding is unknown [see Nonclincal Toxicology (13.1)].

8.4 Pediatric Use

The safety and effectiveness of terazosin have not been established in pediatric patients.

10 OVERDOSAGE

There is limited experience regarding overdosage with terazosin. Following a single oral dose of 300 mg (15 times the maximum recommended human dose of 20 mg), signs and symptoms of ovedosage included hypothermia, bradycardia and hypotension.

Management of overdose leading to hypotension should concentrate on support of the cardiovascular system. Restoration of blood pressure and normalization of heart rate may be accomplished by keeping the patient in the supine position. If this measure is inadequate, shock should first be treated with volume expanders. If necessary, vasopressors should then be used and renal function should be monitored and supported as needed. Close medical supervision and monitoring should continue until the patient recovers. Dialysis is unlikely to be effective as terazosin is highly protein bound.

Consult the National Capital Poison Center (1-800-222-1222 or www.poison.org) for up-to-date guidance and advice regarding a TEZRULY overdosage.

11 DESCRIPTION

TEZRULY (terazosin), an alpha-1-selective adrenoceptor antagonist, is a quinazoline derivative represented by the following chemical name and structural formula:

1-(4-amino-6,7-dimethoxy-2-quinazolinyl)-4-(tetrahydro-2-furoyl)piperazine monohydrochloride dihydrate

Terazosin hydrochloride is racemic and is a white to pale yellow crystalline substance, sparingly soluble in water. The molecular formula is C19H25N5O4. HCl. 2H2O and the molecular weight is 459.92.

TEZRULY (terazosin) oral solution is supplied in one dosage strength containing 1 mg/mL of terazosin (equivalent to 1.1 mg/mL of terazosin hydrochloride) and the following inactive ingredients: anhydrous citric acid, artificial cherry flavor, glycerin, methylparaben, propylparaben, purified water, sodium citrate dihydrate and sucralose.

12 CLINICAL PHARMACOLOGY

12.1 Mechanism of Action

Benign Prostatic Hyperplasia

The symptoms associated with benign prostatic hyperplasia (BPH) are related to bladder outlet obstruction, which is comprised of two underlying components: static and dynamic. The static component is related to an increase in prostate size caused, in part by a proliferation of smooth muscle cells in the prostatic stroma. However, the severity of BPH symptoms and the degree of urethral obstruction do not correlate well with the size of the prostate. The dynamic component is a function of an increase in smooth muscle tone in the prostate and bladder neck. The degree of tone in this area is mediated by the alpha-1-adrenoceptors, which is reent in high density in the prostate stroma, prostatic capsule, prostatic urethra, and bladder neck. Blockade of the alpha-1 receptor decreases urethral resistance and may relieve the obstruction of BPH symptoms and improve urine flow

Hypertension

The mechanism of action of terazosin is selective blockade of the alpha-1 subtype of adrenergic receptors. The antihypertensive effect of terazosin results from a decrease in systemic vascular resistance. In animals, terazosin causes a decrease in blood pressure by decreasing total peripheral vascular resistance. The vasodilatory hypotensive action of terazosin appears to be produced mainly by antagonism of alpha-1 adrenoceptors. Terazosin decreases blood pressure within 15 minutes following oral administration.

12.2 Pharmacodynamics

Benign Prostatic Hyperplasia (BPH)

Administration of terazosin 10 mg to patients with BPH resulted in significant improvement in both symptoms and peak urinary flow rate compared to placebo [see Clinical Studies (14.1)].

Terazosin administration to normotensive men with BPH did not result in a clinically significant blood pressure lowering effect [see Clinical Studies (14.1)].

Hypertension

Terazosin’s antihypertensive effects usually persist throughout the dosing interval (usually 24 hours), with the supine systolic and diastolic responses 5 to 10 mmHg and 3.5 to 8 mmHg greater, respectively than placebo.

Limited data show that the peak blood pressure response measured 2 to 3 hours post-dose is greater than about twice the trough (24 hour) response during chronic administration [see Clinical Studies (14.2)].

12.3 Pharmacokinetics

Absorption

Following a single oral dose administration of TEZRULY in healthy subjects under fasted conditions, the median (range) time to reach peak plasma terazosin levels was 0.67 (0.50 - 1.75) hours. Mean (standard deviation) terazosin Cmax and AUC0-∞ were 27.09 (7.85) ng/mL and 285.62 (74.77) h*ng/mL, respectively.

Effect of Food

No clinically significant differences in TERZULY pharmacokinetics were observed following administration of a high-fat, high calorie meal [995.5 Kcalories; 38.31 g protein, 80.75 g carbohydrate, and 57.7 g fat].

Distribution

Terazosin is 90 to 94% bound to plasma proteins and binding is constant over the clinically observed concentration range.

Elimination

Terazosin has a half-life of approximately 13 hours.

Metabolism

Terazosin has been shown to undergo minimal hepatic first-pass metabolism and nearly all of the circulating dose is in the form of parent drug.

Elimination

Approximately 10% of an orally administered dose is excreted as parent drug in the urine and approximately 20% is excreted in the feces. The remainder is eliminated as metabolites. Overall, approximately 40% of the administered dose is excreted in the urine and approximately 60% in the feces.

Specific Populations

Geriatric Patients

In a study that evaluated the effect of age on terazosin pharmacokinetics, the mean plasma half-lives were 14.0 and 11.4 hours for the age group ≥ 70 years and the age group of 20-39 years, respectively. After oral administration, the plasma clearance decreased by 31.7% in patients ≥ 70 years of age compared to patients 20-39 years of age.

Patients with Renal Impairment

Impaired renal function had no significant effect on the elimination of terazosin. Dosage adjustment to compensate for the drug removal during hemodialysis (approximately 10%) does not appear to be necessary.

Drug Interactions

In a study (n=24) where terazosin and verapamil were co-administered, terazosin’s mean AUC0-24 increased 11% after the first verapamil dose. After 3 weeks of verapamil treatment, terazosin’s mean AUC0-24 increased by 24% with associated increases in Cmax (25%) and Cmin (32%) means and decrease in mean Tmax from 1.3 hours to 0.8 hours. Statistically significant differences were not found in the verapamil level with and without terazosin.

In a study (n=6) where terazosin and captopril were administered concomitantly, plasma disposition of captopril was not influenced by concomitant administration of terazosin and terazosin maximum plasma concentrations increased linearly with dose at steady-state after administration of terazosin plus captopril.

13 NONCLINICAL TOXICOLOGY

13.1 Carcinogenesis & Mutagenesis & Impairment Of Fertility

Carcinogenesis

Terazosin, administered in the feed to rats at doses of 8, 40, and 250 mg/kg/day (48, 240, and 1500 mg/m^2/day), for two years, was associated with a statistically significant increase in benign adrenal medullary tumors of male rats exposed to the 250 mg/kg dose. This dose is 120 times the maximum recommended human dose of 20 mg (12 mg/m^2) on a body surface area basis. Female rats were unaffected. Terazosin was not oncogenic in mice when administered in feed for 2 years at a maximum tolerated dose of 32 mg/kg/day (96 mg/m^2/day; 8 times the maximum recommended human dose on a body surface area basis). The absence of mutagenicity in a battery of tests, of tumorigenicity of any cell type in the mouse carcinogenicity assay, of increased total tumor incidence in either species, and of proliferative adrenal lesions in female rats, suggests a male rat species-specific event. Numerous other diverse pharmaceutical and chemical compounds have also been associated with benign adrenal medullary tumors in male rats without supporting evidence for carcinogenicity in man.

Mutagenesis

Terazosin was devoid of mutagenic potential when evaluated in vivo and in vitro (the Ames test, in vivo cytogenetics, the dominant lethal test in mice, in vivo Chinese hamster chromosome aberration test and V79 forward mutation assay).

Impairment of Fertility

The effect of terazosin on fertility was assessed in a standard fertility/reproductive performance study in which male and female rats were administered oral doses of 8, 30 and 120 mg/kg/day. Four of 20 male rats given 30 mg/kg (180 mg/m^2; 15 times the maximum recommended human dose on a body surface area basis) and five of 19 male rats given 120 mg/kg (720 mg/m^2; 60 times the maximum recommended human dose on a body surface area basis) failed to sire a litter. Testicular weights and morphology were unaffected by treatment. However, vaginal smears at 30 and 120 mg/kg/day appeared to contain less sperm than smears from control matings and good correlation was reported between sperm count and subsequent pregnancy.

13.2 Animal Pharmacology & OR Toxicology

Oral administration of terazosin for one or two years elicited a statistically significant increase in the incidence of testicular atrophy in rats exposed to 40 and 250 mg/kg/day (20 and 120 times the maximum recommended human dose on a body surface area basis), but not in rats exposed to 8 mg/kg/day (4 times the maximum recommended human dose on a body surface area basis). Testicular atrophy was also observed in dogs dosed with 300 mg/kg/day (> 490 times the maximum recommended human dose on a body surface area basis) for three months but not after one year when dosed with 20 mg/kg/day (30 times the maximum recommended human dose on a body surface area basis). This finding has also been seen with prazosin, another alpha-1 adrenergic antagonist.

The disposition of terazosin in animals is qualitatively similar to that in man. In animals, terazosin causes a decrease in blood pressure by decreasing total peripheral vascular resistance. The vasodilatory hypotensive action of terazosin appears to be produced mainly by antagonism of alpha-1-adrenoceptors.

14 CLINICAL STUDIES

14.1 Benign Prostatic Hyperplasia

Terazosin has been studied in 1222 men with symptomatic BPH. In three placebo-controlled studies, symptom evaluation and uroflowmetric measurements were performed approximately 24 hours following dosing. Symptoms were quantified using the Boyarsky Index which evaluated both obstructive (hesitancy, intermittency, terminal dribbling, impairment of size and force of stream, sensation of incomplete bladder emptying) and irritative (nocturia, daytime frequency, urgency, dysuria) symptoms by rating each of the 9 symptoms from 0-3, for a total score of 27 points. Results from these studies indicated that terazosin statistically significantly improved symptoms and peak urine flow rates over placebo (Table 6).

Table 5. Symptom and Uroflowmetry Scores 24 Hours Following Terazosin Dosing in Three Placebo-Controlled Studies in BPH
 |  | Symptom Score (Range 0-27) |  |  |  | Peak Flow Rate (mL/sec)
 |  |  | Mean | Mean |  |  | Mean | Mean
 | N |  | Baseline | Change | (%) | N | Baseline | Change | (%)
Study 1
(10 mg)a
Titration to fixed dose (12 wk)
Placebo | 55 |  | 9.7 | -2.3 | (24) | 54 | 10.1 | +1.0 | (10)
Terazosin | 54 |  | 10.1 | -4.5 | (45)* | 52 | 8.8 | +3.0 | (34)*
Study 2
(2, 5, 10, 20 mg)b
Titration to response (24 wk)
Placebo | 89 |  | 12.5 | -3.8 | (30) | 88 | 8.8 | +1.4 | (16)
Terazosin | 85 |  | 12.2 | -5.3 | (43)* | 84 | 8.4 | +2.9 | (35)*
Study 3
(1, 2, 5, 10 mg)c
Titration to response (24 wk)
Placebo | 74 |  | 10.4 | -1.1 | (11) | 74 | 8.8 | +1.2 | (14)
Terazosin | 73 |  | 10.9 | -4.6 | (42)* | 73 | 8.6 | +2.6 | (30)*

a Highest dose 10 mg shown.

b 23% of patients on 10 mg, 41% of patients on 20 mg.

c 67% of patients on 10 mg.

* Significantly (p ≤ 0.05) more improvement than placebo.

In all three studies, both symptom scores and peak urine flow rates showed statistically significant improvement from baseline in patients treated with terazosin from week 2 (or the first clinic visit) and throughout the study duration.

Analysis of the effect of terazosin on individual urinary symptoms demonstrated that terazosin significantly improved the symptoms of hesitancy, intermittency, impairment in size and force of urinary stream, sensation of incomplete emptying, terminal dribbling, daytime frequency and nocturia, compared to placebo.

Global assessments of overall urinary function and symptoms were also performed by investigators who were blinded to patient treatment assignment. In Studies 1 and 3, patients treated with terazosin had a significantly (p ≤ 0.001) greater overall improvement compared to placebo treated patients.

In a short-term study (Study 1), patients were randomized to either 2, 5 or 10 mg of terazosin or placebo. Patients randomized to the 10 mg group achieved a statistically significant response in both symptoms and peak flow rate compared to placebo (Figure 1).

Figure 1
Study 1
Mean Change in Total Symptom Score from Baseline^+ | Mean Increase in Peak Flow Rate (mL/sec) from Baseline^+
+ for baseline values see above table; * p ≤ 0.05, compared to placebo group

In a long-term, open-label, non-placebo controlled clinical trial, 181 men were followed for 2 years and 58 of these men were followed for 30 months. The effect of terazosin on urinary symptom scores and peak flow rates was maintained throughout the study duration (Figures 2 and 3):

Figure 2

Mean Change in Total Symptom Score from Baseline

Long-Term, Open-Label, Non-Placebo Controlled Study (N=494)

*p ≤ 0.05 vs. baseline; mean baseline = 10.7

Figure 3

Mean Change in Peak Flow Rate from Baseline

Long-Term, Open-Label, Non-Placebo Controlled Study (N=494)

* p ≤ 0.05 vs. baseline; mean baseline = 9.9

In this long-term trial, both symptom scores and peak urinary flow rates showed statistically significant improvement suggesting a relaxation of smooth muscle cells.

Although antagonism of alpha-1-adrenoceptors also lowers blood pressure in hypertensive patients with increased peripheral vascular resistance, terazosin treatment of normotensive men with BPH did not result in a clinically significant blood pressure lowering effect (Table 6).

Table 6. Mean Changes in Blood Pressure from Baseline to Final Visit in all Double-Blind, Placebo-Controlled Studies
 |  | Normotensive Patients DBP ≤ 90 mm Hg |  | Hypertensive Patients DBP > 90 mm Hg
 | Group | N | Mean Change | N | Mean Change
SBP | Placebo | 293 | -0.1 | 45 | -5.8
(mm Hg) | Terazosin | 519 | -3.3* | 65 | -14.4*
DBP | Placebo | 293 | +0.4 | 45 | -7.1
(mm Hg) | Terazosin | 519 | -2.2* | 65 | -15.1*
* p ≤ 0.05 vs. placebo

14.2 Hypertension

Patients in clinical trials of terazosin were administered once daily (the great majority) and twice daily regimens with total doses usually in the range of 5 to 20 mg/day, and had mild (about 77%, diastolic pressure 95 to 105 mmHg) or moderate (23%, diastolic pressure 105 to 115 mmHg) hypertension. Because terazosin, like all alpha-1 adrenergic antagonists can cause unusually large falls in blood pressure after the first dose or first few doses, the initial dose was 1 mg in virtually all trials, with subsequent titration to a specified fixed dose or titration to some specified blood pressure end point (usually a supine diastolic pressure of 90 mmHg).

Blood pressure responses were measured at the end of the dosing interval (usually 24 hours) and effects were shown to persist throughout the interval, with the usual supine responses 5 to 10 mmHg systolic and 3.5 to 8 mmHg diastolic greater than placebo. The responses in the standing position tended to be somewhat larger, by 1 to 3 mmHg, although this was not true in all studies. The magnitude of the blood pressure responses was similar to prazosin and less than hydrochlorothiazide (in a single study of hypertensive patients). In measurements 24 hours after dosing, heart rate was unchanged.

Limited measurements of peak response (2-3 hours after dosing) during chronic terazosin administration indicate that it is greater than about twice the trough (24 hour) response, suggesting some attenuation of response at 24 hours, presumably due to a fall in blood terazosin concentrations at the end of the dose interval. This explanation is not established with certainty, however, and is not consistent with the similarity of blood pressure response to once daily and twice daily dosing and with the absence of an observed dose-response relationship over a range of 5-20 mg, i.e., if blood concentrations had fallen to the point of providing less than full effect at 24 hours, a shorter dosing interval or larger dose should have led to increased response.

Blood pressure should be measured at the end of the dose interval; if response is not satisfactory, patients may be tried on a larger dose or twice daily dosing regimen. The latter should also be considered if blood pressure-related side effects, such as dizziness, palpitations, or orthostatic complaints are seen within a few hours after dosing.

The greater blood pressure effect associated with peak plasma concentrations (first few hours after dosing) appears somewhat more position-dependent (greater in the erect position) than the effect of terazosin at 24 hours and in the erect position there is also a 6-10 beat per minute increase in heart rate in the first few hours after dosing.

During the first 3 hours after dosing, 12.5% of patients had a systolic pressure fall of 30 mmHg or more from supine to standing, or standing systolic pressure below 90 mmHg with a fall of at least 20 mmHg, compared to 4% of a placebo group.

There was a tendency for patients to gain weight during terazosin therapy. In placebo-controlled monotherapy trials, male and female patients receiving terazosin gained a mean of 1.7 and 2.2 pounds respectively, compared to losses of 0.2 and 1.2 pounds respectively in the placebo group. Both differences were statistically significant.

During controlled clinical trials, patients receiving terazosin monotherapy had a small but statistically significant decrease (a 3% fall) compared to placebo in total cholesterol and the combined low-density and very-low-density lipoprotein fractions. No significant changes were observed in high-density lipoprotein fraction and triglycerides compared to placebo.

Analysis of clinical laboratory data following administration of terazosin suggested the possibility of hemodilution based on decreases in hematocrit, hemoglobin, white blood cells, total protein and albumin. Decreases in hematocrit and total protein have been observed with alpha-1-adrenoceptors antagonism and are attributed to hemodilution.

16 HOW SUPPLIED/STORAGE AND HANDLING

How Supplied

TEZRULY 1 mg/mL oral solution is a clear, cherry flavored solution, free from visible particulate matter available in bottles of 150 mL with child resistant closure, NDC 70954-592-10.

Storage and Handling

Store at 20°C to 25°C (68°F to 77°F); excursions permitted to 15°C to 30°C (59°F to 86°F) [see USP Controlled Room Temperature].

Keep the container tightly closed.

17 PATIENT COUNSELING INFORMATION

Advise the patient to read the FDA-approved patient labeling (Patient Information).

Administration Instructions

Inform patients that a calibrated measuring device, such as an oral syringe or oral dosing cup, should be obtained from the pharmacy to measure and deliver the prescribed dose accurately. A household measuring cup, teaspoon, or tablespoon is not an adequate measuring device.

Syncope and ‘‘First-dose’’ Effect and Orthostatic Hypotension

Inform patients about the possibility of syncopal and orthostatic symptoms, especially at the initiation of therapy, and to avoid driving or hazardous tasks for 12 hours after the first dose, after a dosage increase and after more than a few days of interruption of therapy when treatment is resumed. They should be cautioned to avoid situations where injury could result should syncope occur during initiation of terazosin therapy, including driving, operating machinery and performing hazardous tasks. They should also be advised of the need to sit or lie down when symptoms of lowered blood pressure occur, although these symptoms are not always orthostatic, and to be careful when rising from a sitting or lying position. If dizziness, lightheadedness, or palpitations are bothersome, advise patients to report these symptoms to their healthcare provider, so that dose adjustment can be considered. Inform patients that drowsiness or somnolence can occur with terazosin, requiring caution in people who must drive or operate heavy machinery [see Warnings and Precautions (5.1, 5.2)].

Risk of Hypotension when Tezruly is Taken Concomitantly with Other Antihypertensive Agents and/or Phosphodiesterase Type 5 Inhibitors (PDE5-I)

Advise patients that dosage reduction of their other antihypertensive agents and/or PDE5-I may be necessary to avoid the possibility of developing significant hypotension.

Priapism

Advise the patient about the possibility of priapism as a result of treatment with TEZRULY and other similar medications. Patients should be informed that this reaction is extremely rare, but if not brought to immediate medical attention, can lead to permanent erectile dysfunction (impotence) [see Warnings and Precautions (5.3)].

Screening for Prostate Cancer

Advise patients that prostate cancer and BPH frequently present with many of the same symptoms and may co-exist; therefore, inform patients that they should have screening for the presence of prostate cancer prior to treatment with TEZRULY and at regular intervals afterwards [see Warnings and Precautions (5.4)].

Intraoperative Floppy Iris Syndrome

Advise the patient when considering cataract surgery to tell their ophthalmologist that they have taken TEZRULY [see Warnings and Precautions (5.5)].

Trademarks are the property of their respective owners.

Distributed by:

ANI Pharmaceuticals, Inc.

Baudette, MN 56623

Issued: 07/2024

LB4752-01

TEZRULYTM is a pending trademark of ANI Pharmaceuticals, Inc.

PATIENT INFORMATION

TEZRULY (tez-ROO-lee) (terazosin)
oral solution

What is TEZRULY?
TEZRULY is a prescription medicine that contains terazosin hydrochloride and is called an “alpha-blocker”. TEZRULY is used to treat:

- the symptoms of benign prostatic hyperplasia (BPH)
- high blood pressure (hypertension)

It is not known if TEZRULY is safe and effective in children.

Do not take TEZRULY if you:
are allergic to terazosin or any of the ingredients in TEZRULY. See the end of this Patient Information leaflet for a complete list of ingredients in TEZRULY.

Before taking TEZRULY, tell your healthcare provider about all of your medical conditions, including if you:

- have had low blood pressure, especially after taking other medicine. Signs of low blood pressure include fainting, dizziness, and lightheadedness.
- have any planned eye surgery.
- have prostate cancer or a history of prostate cancer. Your healthcare provider may have you checked for prostate cancer before you start taking and while you take TEZRULY.
- are pregnant or plan to become pregnant. It is not known if TEZRULY will harm your unborn baby.
- are breastfeeding or plan to breastfeed. It is not known if TEZRULY passes into your breastmilk. Talk to your healthcare provider about the best way to feed your baby if you take TEZRULY.

Tell your healthcare provider about all the medicines you take, including prescription and over-the-counter medicines, vitamins, and herbal supplements. TEZRULY may affect the way other medicines work, and other medicines may affect the way TEZRULY works causing side effects.
Especially tell your healthcare provider if you take:

- other medicine for high blood pressure, particularly the calcium channel blocker verapamil. The use of TEZRULY with verapamil can lead to a drop in blood pressure or to fainting.
- medicines to treat erectile dysfunction (ED) called phosphodiesterase type 5 (PDE-5) inhibitors. The use of TEZRULY with PDE-5 inhibitors can lead to a drop in blood pressure or to fainting.

Know your medicines. Keep a list to show your healthcare providers or pharmacist when you get a new medicine.

How should I take TEZRULY?

- Take TEZRULY by mouth with or without food.
- The starting dose of TEZRULY is 1 mg (1 mL) at bedtime. Do not take more than 1 mg as your starting dose. This is to reduce the chance of a sudden drop in blood pressure which can cause fainting, dizziness, and lightheadedness. Your healthcare provider will then increase your dose of TEZRULY as needed.
- Your healthcare provider will tell you how much TEZRULY to take and when to take it.
- Your healthcare provider may need to change your dose of TEZRULY until it is the right dose for you.

- Take TEZRULY using a marked (calibrated) measuring device, such as an oral syringe or oral dosing cup. Ask your pharmacist for a measuring device and instructions on how to measure and take the correct dose of medicine. A household measuring cup, teaspoon, or tablespoon is not an adequate measuring device.

What should I avoid while taking TEZRULY?
Do not drive or perform any hazardous task until at least 12 hours after you have taken TEZRULY if you are taking:

- your first dose of TEZRULY
- TEZRULY for the first time after your healthcare provider has increased your dose of TEZRULY
- TEZRULY for the first time after any breaks (interruptions) in your treatment with TEZRULY

What are the possible side effects of TEZRULY?
TEZRULY may cause serious side effects, including:

- A sudden drop in blood pressure, especially when you first start treatment or when there is an increase in your dose of TEZRULY, is common but can also be serious. This may cause you to have a feeling that your heart is pounding or racing (palpitations), faint, have a spinning feeling (vertigo), or to feel dizzy or lightheaded. If you have a spinning feeling, dizziness or lightheadedness, you should sit or lie down and be careful when rising from a sitting or lying position. Your risk of having this problem may be increased if you take TEZRULY with certain other medicines that lower blood pressure including verapamil and PDE-5 inhibitors. Your healthcare provider may monitor your blood pressure while you take TEZRULY. See “What should I avoid while taking TEZRULY?”
- A painful erection that will not go away. TEZRULY can cause a painful erection (priapism), which cannot be relieved by having sex or masturbation. If this happens, get medical help right away. If priapism is not treated, you may not be able to get an erection in the future
- Eye problems during cataract surgery. A condition called Intraoperative Floppy Iris Syndrome (IFIS) can happen during cataract surgery if you take or have taken alpha-blockers such as TEZRULY. If you need to have cataract surgery, be sure to tell your ophthalmologist (eye doctor) if you take or have taken TEZRULY.

The most common side effects of TEZRULY include:

- weakness
- dizziness
- puffy feet or hands
- lack of energy
- nasal congestion
- drowsiness

These are not all the possible side effects of TEZRULY.
Call your doctor for medical advice about side effects. You may report side effects to FDA at 1-800-FDA-1088.

General information about the safe and effective use of TEZRULY.
Medicines are sometimes prescribed for purposes other than those listed in a Patient Information leaflet. Do not use TEZRULY for a condition for which it was not prescribed. Do not give TEZRULY to other people, even if they have the same symptoms you have. It may harm them.
You can ask your healthcare provider or pharmacist for information that is written for health professionals.

What are the ingredients in TEZRULY?
Active ingredient: terazosin hydrochloride
Inactive ingredients: artificial cherry flavor, citric acid anhydrous, glycerin, methylparaben, propylparaben, purified water, sodium citrate dihydrate and sucralose.

Distributed by:
ANI Pharmaceuticals, Inc.
Baudette, MN 56623
TEZRULYTM is a pending trademark of ANI Pharmaceuticals, Inc.
For more information, call 1-855-204-1431.

This Patient Information has been approved by the U.S. Food and Drug Administration.

Issued: 07/2024

LB4752-01

PACKAGE LABEL.PRINCIPAL DISPLAY PANEL

TEZRULY (terazosin) Oral Solution, 1 mg/mL

NDC 70954-592-10 - 150 mL per bottle